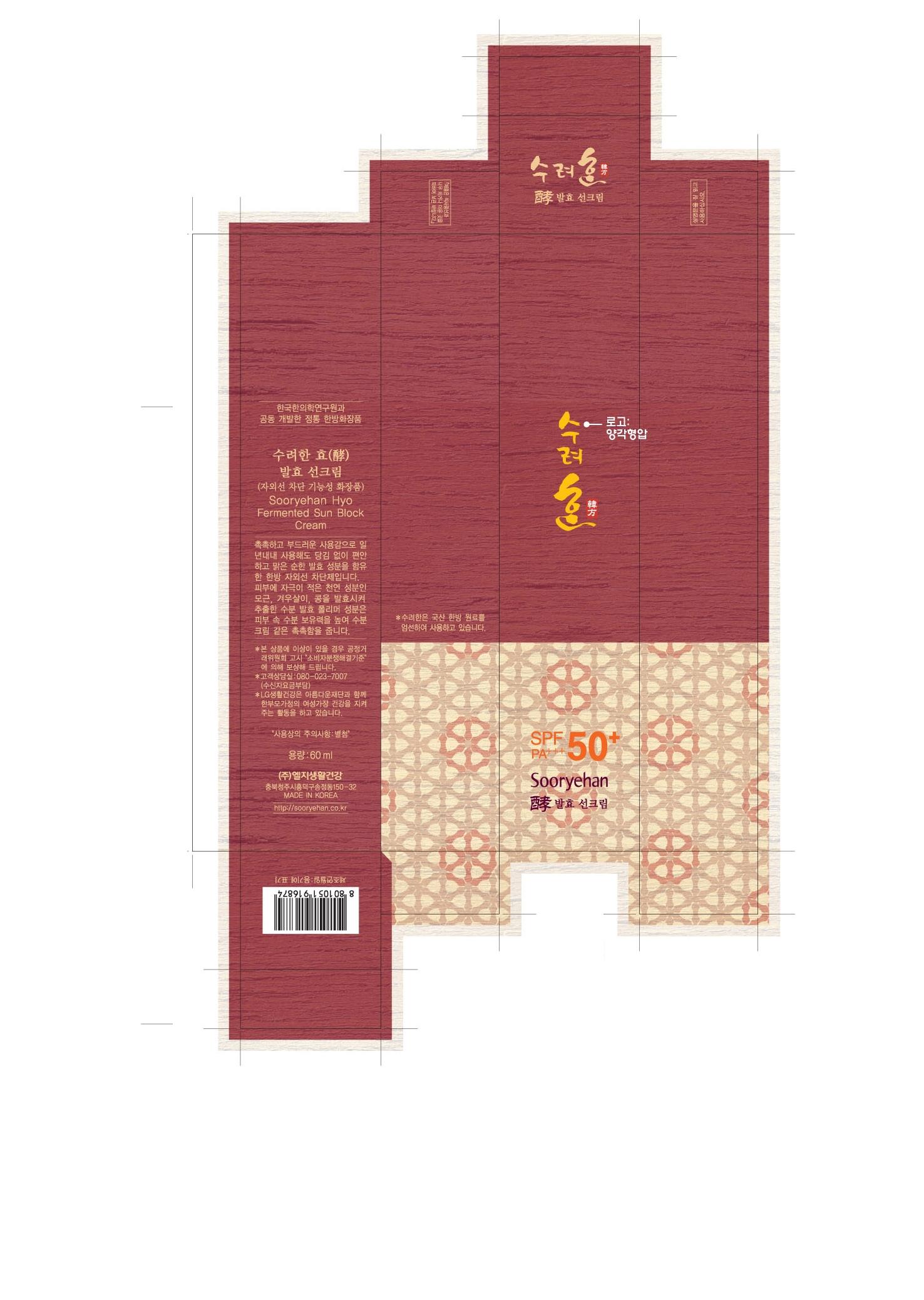 DRUG LABEL: SOORYEHAN HYO FERMENTED SUN BLOCK
NDC: 53208-549 | Form: CREAM
Manufacturer: LG Household and Healthcare, Inc.
Category: otc | Type: HUMAN OTC DRUG LABEL
Date: 20110928

ACTIVE INGREDIENTS: OCTINOXATE 7 mL/100 mL; TITANIUM DIOXIDE 2.52 mL/100 mL; AMILOXATE 1.6 mL/100 mL; BEMOTRIZINOL 1 mL/100 mL; DIETHYLAMINO HYDROXYBENZOYL HEXYL BENZOATE 1 mL/100 mL; ENSULIZOLE 3.9 mL/100 mL; TROMETHAMINE 2.63 mL/100 mL
INACTIVE INGREDIENTS: WATER; CYCLOMETHICONE; CYCLOMETHICONE 5; ALUMINUM HYDROXIDE; STEARIC ACID; HYDROGENATED SOYBEAN LECITHIN; PEG-10 RAPESEED STEROL; GLYCERIN; C14-22 ALCOHOLS; SQUALANE; MACADAMIA OIL; TRIETHYLHEXANOIN; ARACHIDYL GLUCOSIDE; SHEA BUTTER; 1,2-HEXANEDIOL; GLYCERYL MONOSTEARATE; CERAMIDE 3; CHOLESTEROL; PEG-100 STEARATE; DIMETHICONE; TROMETHAMINE; DIPROPYLENE GLYCOL; MEDIUM-CHAIN TRIGLYCERIDES; PEG-100 STEARATE; CETYL PHOSPHATE; PANTHENOL; PONCIRUS TRIFOLIATA FRUIT; DIOSPYROS KAKI LEAF; CHINESE CINNAMON; ARTEMISIA PRINCEPS LEAF; CHRYSANTHELLUM INDICUM TOP; CHAENOMELES SPECIOSA FRUIT; GREEN TEA LEAF; TROLAMINE; METHYLPARABEN; XANTHAN GUM; PUERARIA MONTANA VAR. LOBATA ROOT; BLACK COHOSH; POMEGRANATE; SCHISANDRA CHINENSIS FRUIT; ANGELICA GIGAS ROOT; PATCHOULI OIL; PRUNUS ARMENIACA SEED; LIGUSTICUM TENUISSIMUM ROOT; MUNG BEAN; ASIAN GINSENG; CAROB; TRICHOSANTHES KIRILOWII ROOT; ETHYLPARABEN; PROPYLPARABEN; EDETATE TRISODIUM; FD&C YELLOW NO. 5; FD&C YELLOW NO. 6

SOORYEHAN HYO FERMENTED SUN BLOCK CREAM

ACTIVE INGREDIENT

OCTINOXATE 7ml
TITANIUM DIOXIDE 2.52ml
AMILOXATE 1.6ml
BEMOTRIZINOL 1ml
DIETHYLAMINO HYDROXYBENZOYL HEXYL BENZOATE 1ml
ENSULIZOLE 3.9ml
TROMETHAMINE 2.63ml

WARNINGS AND PRECAUTIONS

For external use only.

KEEP OUT OF REACH OF CHILDREN

If swallowed, get medical help or contact a Poison Control Center right away.

Stop use if a rash or irritation develops and lasts.

WHEN USING

Keep out of eyes. Rinse with water to remove.

PACKAGE LABEL

SRH HYO FERMENTED SUN BLOCK CREAM

INACTIVE INGREDIENT

Enter section text here